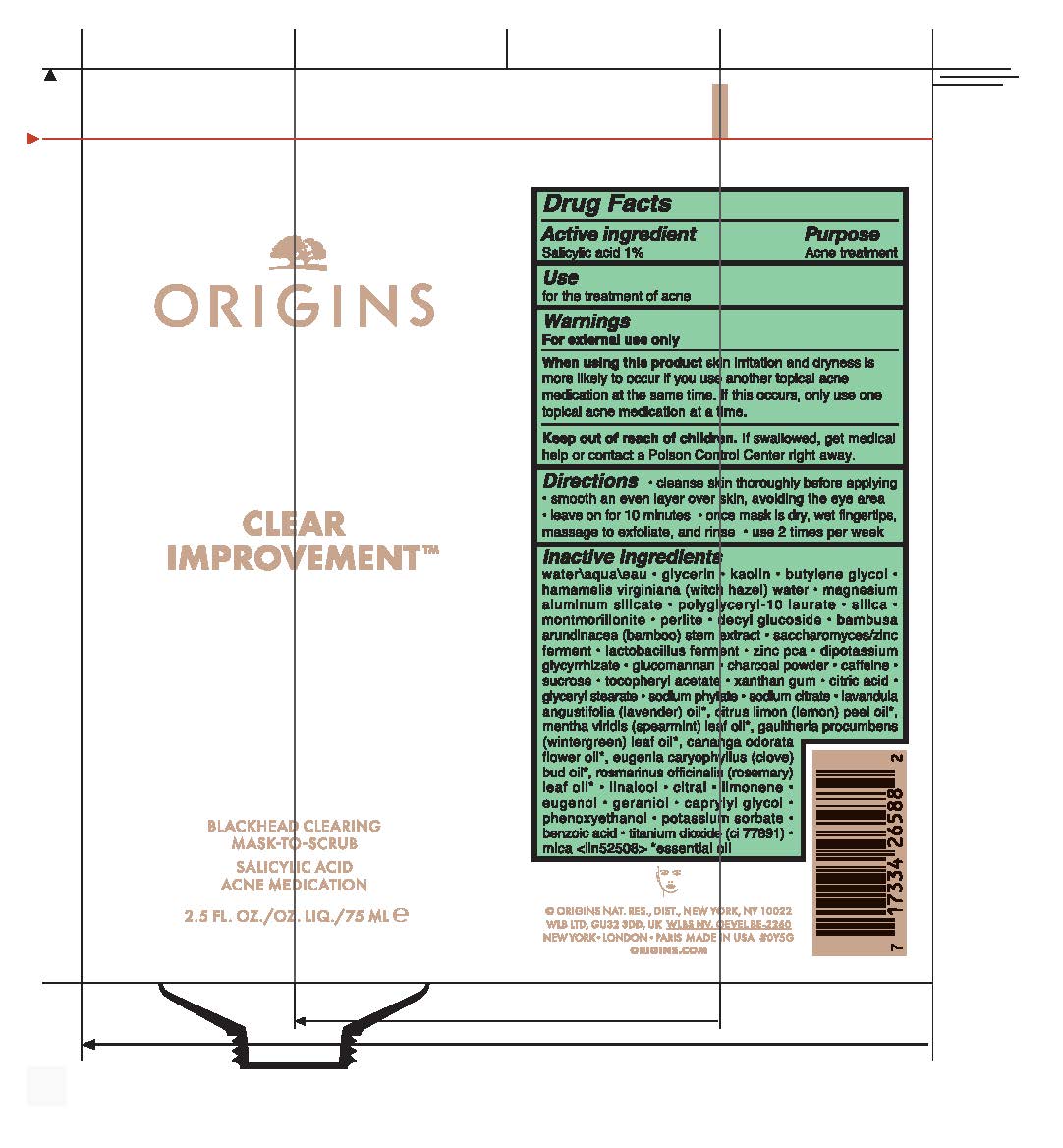 DRUG LABEL: CLEAR IMPROVEMENT BLACKHEAD CLEARING MASK TO SCRUB
NDC: 59427-118 | Form: LIQUID
Manufacturer: ORIGINS NATURAL RESOURCES INC.
Category: otc | Type: HUMAN OTC DRUG LABEL
Date: 20240205

ACTIVE INGREDIENTS: SALICYLIC ACID 10 mg/1 mL
INACTIVE INGREDIENTS: SUCROSE; GLYCERYL MONOSTEARATE; CANANGA OIL; TITANIUM DIOXIDE; MICA; BUTYLENE GLYCOL; SPEARMINT OIL; CITRAL; METHYL SALICYLATE; SODIUM CITRATE; MONTMORILLONITE; ALPHA-TOCOPHEROL ACETATE; ZINC PIDOLATE; LAVENDER OIL; LIMONENE, (+)-; GERANIOL; GLYCERIN; KAOLIN; HAMAMELIS VIRGINIANA TOP WATER; POLYGLYCERYL-10 LAURATE; BAMBUSA BAMBOS STEM; GLYCYRRHIZINATE DIPOTASSIUM; ACTIVATED CHARCOAL; XANTHAN GUM; EUGENOL; POTASSIUM SORBATE; PERLITE; CAFFEINE; CITRIC ACID MONOHYDRATE; LAUROYL LYSINE; LEMON OIL; ROSEMARY OIL; LINALOOL, (+/-)-; PHENOXYETHANOL; KONJAC MANNAN; WATER; MAGNESIUM ALUMINUM SILICATE; SILICON DIOXIDE; DECYL GLUCOSIDE; CLOVE OIL; CAPRYLYL GLYCOL; BENZOIC ACID

CLEAR IMPROVEMENT BLACKHEAD CLEARING MASK TO SCRUB

Active Ingredient

Salicylic Acid 1%

Purpose

Acne Treatment

Use

for the treatmenet of acne

Warnings

For External use only

When using this product

skin irritattion and dryness is more likely to occur if you use another topical acne medication at the same time. If this occurs, only use one topical acne medication at a time.

Keep out of reach of children

If swallowed, get medical help or contact a poison control center right away.

Directions

- cleanse skin throughly before applying
- smooth an even layer over skin, avoiding the eye area
- leave on for 10 minutes
- once mask is dry, we fingertips, massage to exfoliate, and ronse
- use 2 times per week

Inactive Ingredients

water\aqua\eau,glycerin,kaolin,butylene glycol,hamamelis virginiana (witch hazel) water,magnesium aluminum silicate,polyglyceryl-10 laurate,silica,montmorillonite,perlite,decyl glucoside,bambusa arundinacea (bamboo) stem extract,saccharomyces/zinc ferment,lactobacillus ferment,zinc pca,dipotassium glycyrrhizate,glucomannan,charcoal powder,caffeine,sucrose,tocopheryl acetate,xanthan gum,citric acid,glyceryl stearate,sodium phytate,sodium citrate,lavandula angustifolia (lavender) oil*, citrus limon (lemon) peel oil*, mentha viridis (spearmint) leaf oil*, gaultheria procumbens (wintergreen) leaf oil*, cananga odorata flower oil*, eugenia caryophyllus (clove) bud oil*, rosmarinus officinalis (rosemary) leaf oil*,linalool,citral,limonene,eugenol,geraniol,caprylyl glycol,phenoxyethanol,potassium sorbate,benzoic acid,titanium dioxide (ci 77891),mica <iln52508>
* essential oil

PACKAGE LABEL

ORIGINS

CLEAR IMPROVEMENT

BLACKHEAD CLEARING

MASK-TO-SCRUB

SALICYLIC ACID

ACNE MEDICATION

2.5 FL.OZ/OZ. LIQ/75ML E